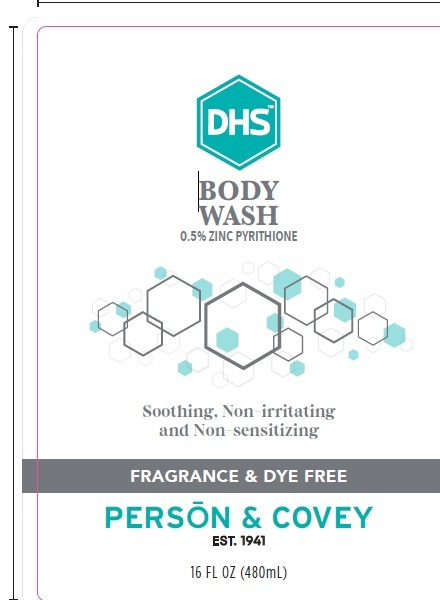 DRUG LABEL: DHS Body Wash
NDC: 0096-0742 | Form: LIQUID
Manufacturer: Person and Covey
Category: otc | Type: HUMAN OTC DRUG LABEL
Date: 20251223

ACTIVE INGREDIENTS: ZINC PYRITHIONE 50 mg/1 mL
INACTIVE INGREDIENTS: SODIUM CHLORIDE; HYDROXYPROPYL METHYLCELLULOSE; SODIUM HYDROXIDE; TRIETHANOLAMINE LAURYL SULFATE; CITRIC ACID; MAGNESIUM ALUMINUM SILICATE TYPE IA; WATER; PEG-8 DISTEARATE; COCAMIDOPROPYL HYDROXYSULTAINE

DHS Body Wash

Warnings

For external use only.

When using this product

- avoid contact with eyes
- If contact occurs, rinse thoroughly with water
- stop use if condition worsens or does not improve after regular use

Stop and ask a doctor if

- condition covers a large area.
- condition worsens or does not improve after regular use.

Inactive Ingredients

Water (Agua) , Triethanolamine, Laurel Sulfate, Cocamidopropyl, Hydroxysultaine, Magnesium Aluminum Silicate,
Sodium chloride, PEG-8 Distearate, Hydroxypropyl Methylcellulose, Magnesium Aluminum Silicate, Citric Acid, Sodium Hydroxide.

Keep out of the reach of children.

If swallowed, get medical help or contact a Poison Control Center right away.

Active ingredient

Zinc Pyrithione 0.5%

Purpose

Skin protectant / Anti-seborrheic

Use

- helps control and reduce the symptoms of seborrheic dermatitis.
- helps relieve flaking, scaling, redness, and itching
- helps prevent recurrence when used regularly
- Store away from excessive heat or cold.

Dosage and Administration

Directions

use daily or as directed by a doctor.
apply to wet skin.
massage into affected area.
leave on skin for several minutes
rinse thoroughly